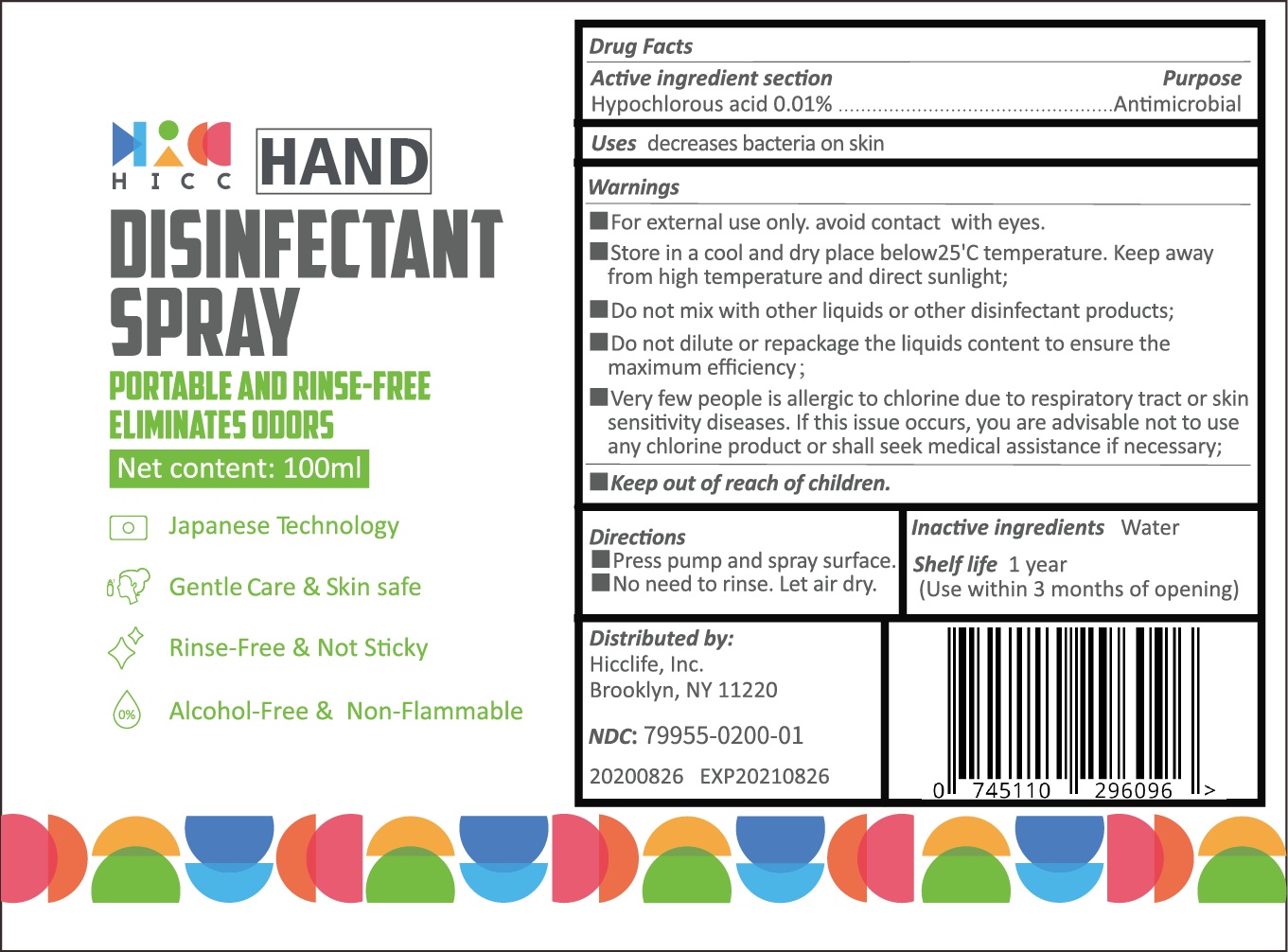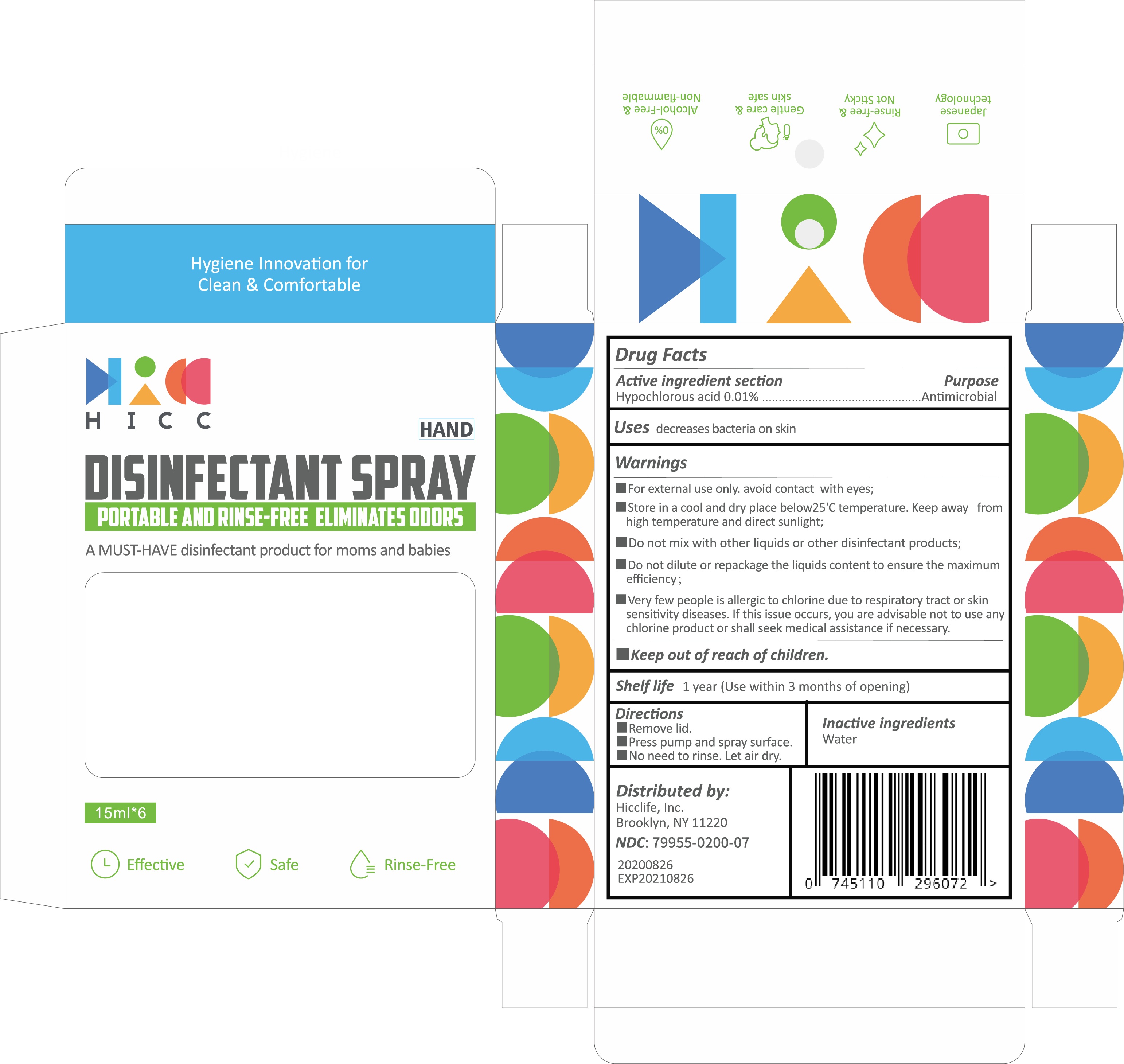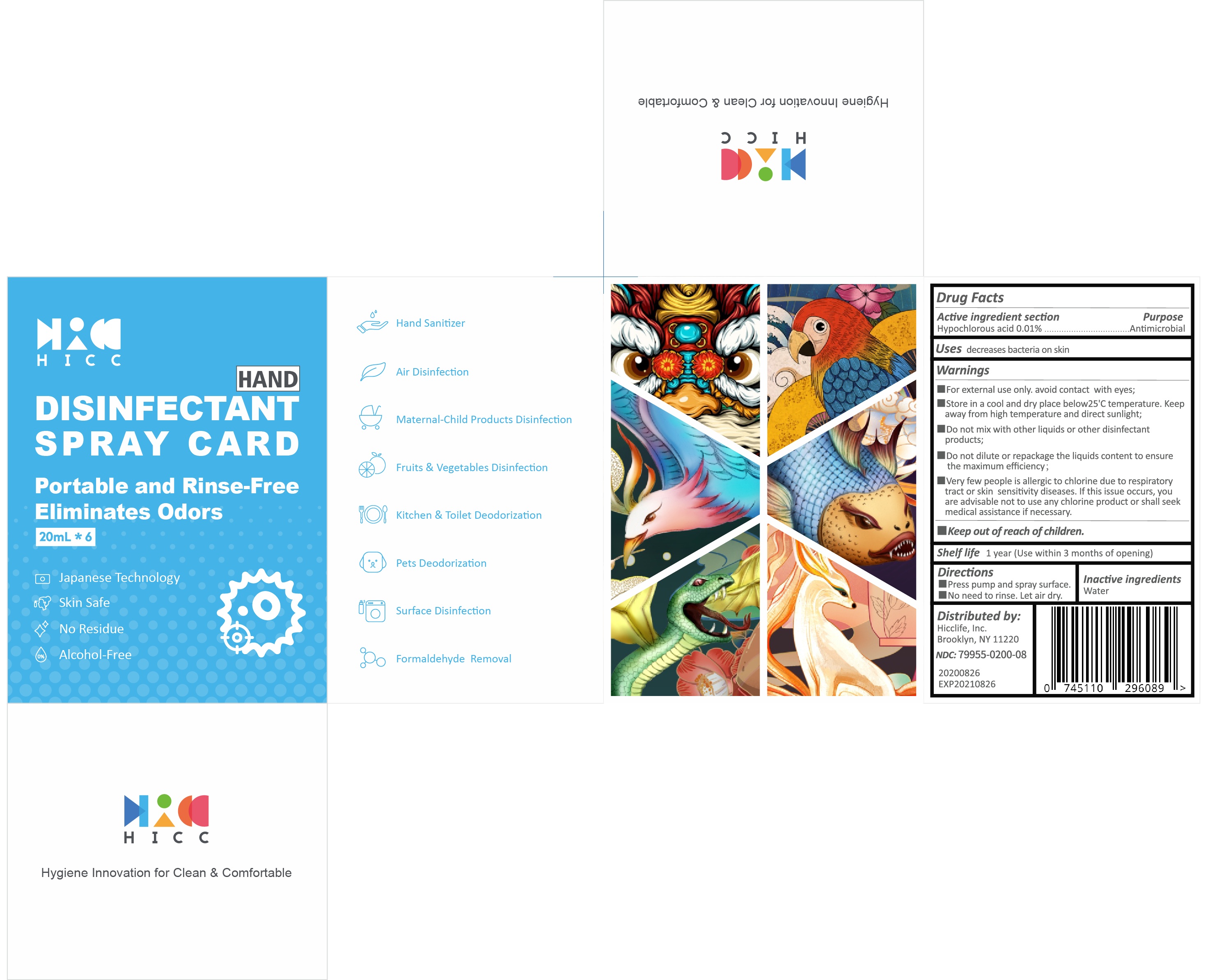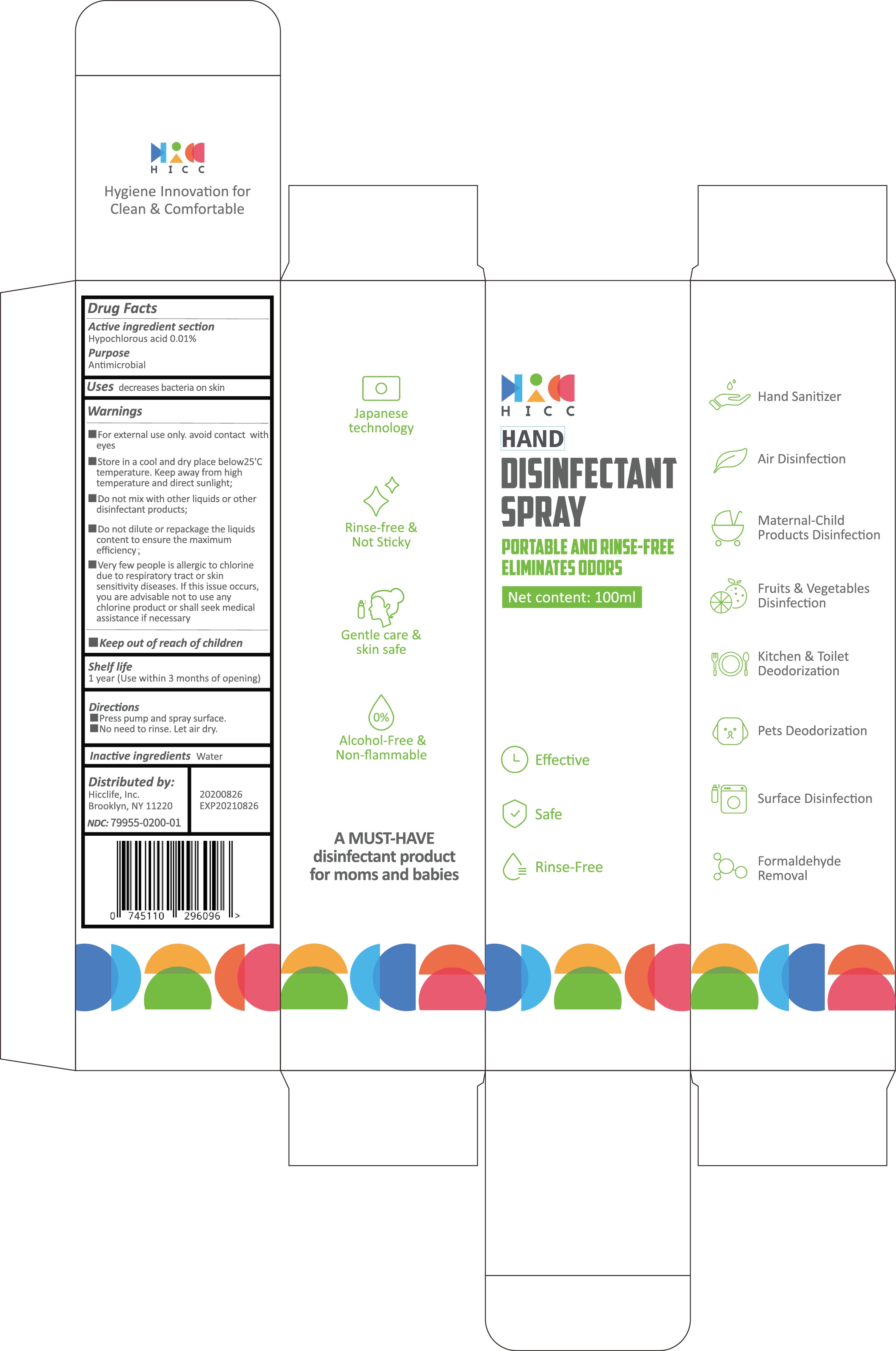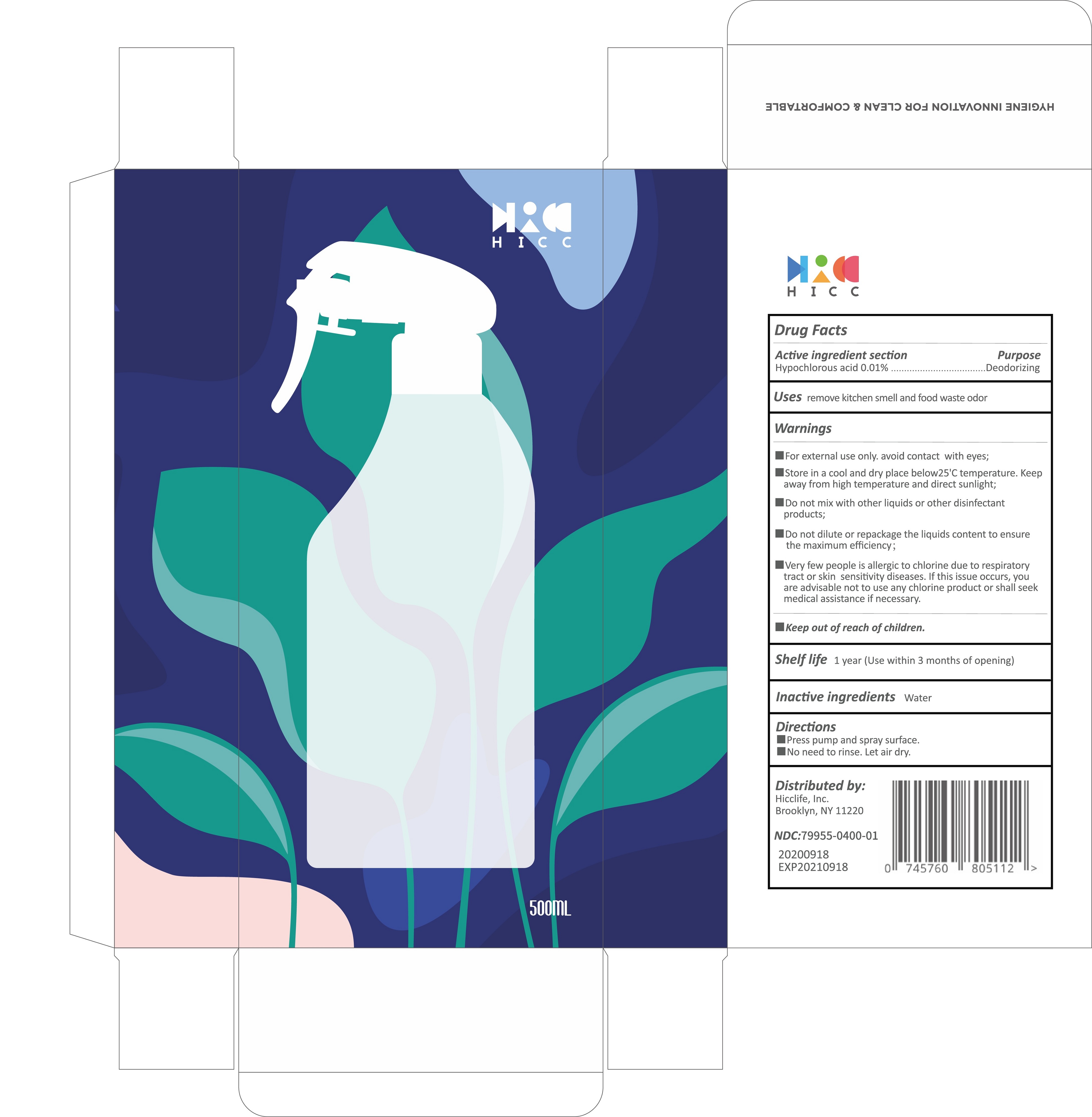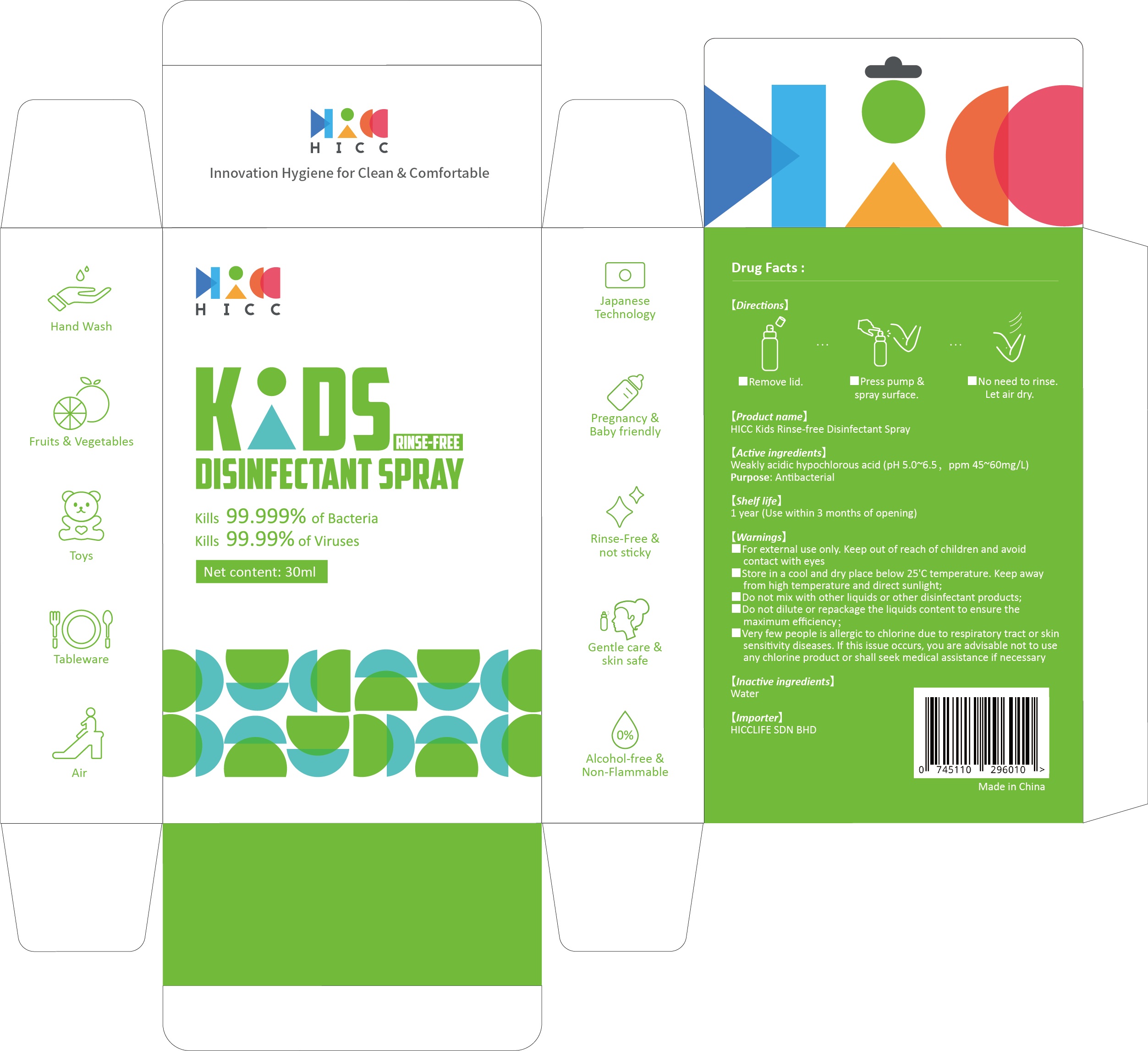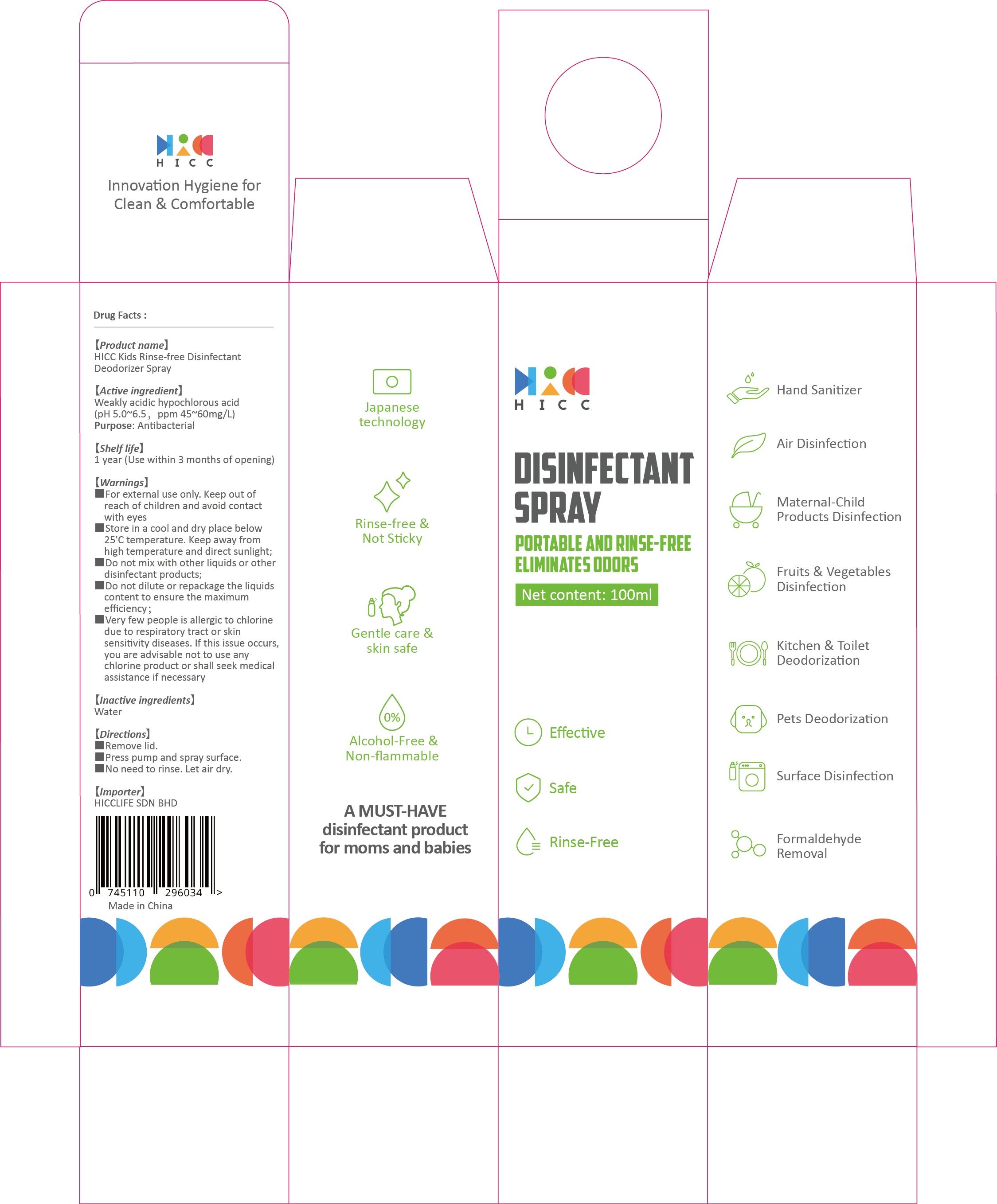 DRUG LABEL: HICC Kitchen Deodorizer
NDC: 79955-300 | Form: SPRAY
Manufacturer: Qianxun Everything (Shenzhen) Technology Co., Ltd.
Category: otc | Type: HUMAN OTC DRUG LABEL
Date: 20200917

ACTIVE INGREDIENTS: HYPOCHLOROUS ACID 0.06 mg/100 mL
INACTIVE INGREDIENTS: WATER

Active Ingredient……………………hypochlorous acid（45~60mg/L）

INACTIVE INGREDIENT

Water

DOSAGE AND ADMINISTRATION

- Remove lid
- Press pump&spray surface
- No need to rinse, Let air dry.

WARNINGS

- Store in a cool and dry place below 25℃ temperature. Keep away from high temperature and direct sunlight.
- Very few people is allergic to chlorine due to respiratory tract or skin sensitivity diseases, if this issue occurs. you are advisable not to use any chorine product or shall seek medical assistance if necessary

KEEP OUT OF REACH OF CHILDREN

For external use only. Keep out of reach of children and avoid contact with eyes.

DO NOT USE

- Do not mix with other liquids or other disinfectant products:
- Do not dilute or repackage the liquids content to ensure the maximum efficiency: